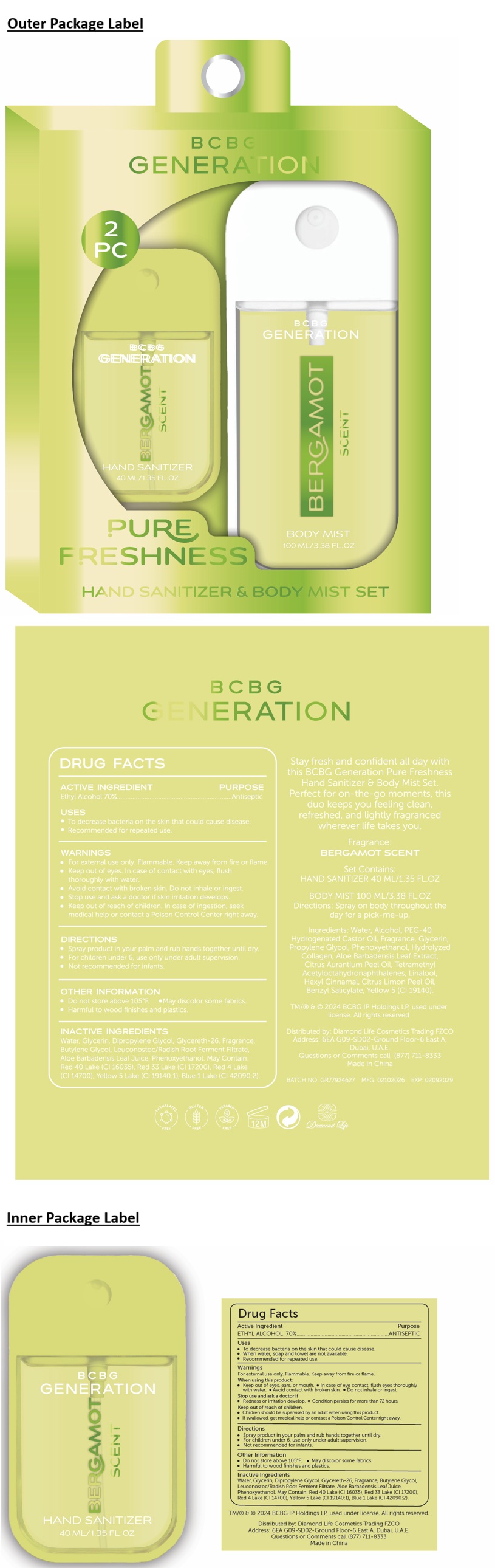 DRUG LABEL: BCBG GENERATION HAND SANITIZER BERGAMOT SCENT
NDC: 87247-428 | Form: SPRAY
Manufacturer: Diamond Life Cosmetics Trading FZCO
Category: otc | Type: HUMAN OTC DRUG LABEL
Date: 20260213

ACTIVE INGREDIENTS: ALCOHOL 70 mL/100 mL
INACTIVE INGREDIENTS: WATER; GLYCERIN; DIPROPYLENE GLYCOL; GLYCERETH-26; BUTYLENE GLYCOL; LEUCONOSTOC/RADISH ROOT FERMENT FILTRATE; ALOE VERA LEAF JUICE; PHENOXYETHANOL; FD&C RED NO. 40 ALUMINUM LAKE; D&C RED NO. 33; FD&C RED NO. 4; FD&C YELLOW NO. 5 ALUMINUM LAKE; FD&C BLUE NO. 1 ALUMINUM LAKE

BCBG GENERATION HAND SANITIZER BERGAMOT SCENT

ACTIVE INGREDIENT

Ethyl Alcohol 70%

PURPOSE

Antiseptic

USES

• To decrease bacteria on the skin that could cause disease.
• Recommended for repeated use.

WARNINGS

• For external use only. Flammable. Keep away from fire or flame.
• Keep out of eyes. In case of contact with eyes, flush thoroughly with water.
• Avoid contact with broken skin. Do not inhale or ingest.
• Stop use and ask a doctor if skin irritation develops.

• Keep out of reach of children. In case of ingestion, seek medical help or contact a Poison Control Center right away.

DIRECTIONS

• Spray product in your palm and rub hands together until dry.
• For children under 6, use only under adult supervision.
• Not recommended for infants.

OTHER INFORMATION

• Do not store above 105°F. • May discolor some fabrics.
• Harmful to wood finishes and plastics.

INACTIVE INGREDIENTS

Water, Glycerin, Dipropylene Glycol, Glycereth-26, Fragrance, Butylene Glycol, Leuconostoc/Radish Root Ferment Filtrate, Aloe Barbadensis Leaf Juice, Phenoxyethanol. May Contain: Red 40 Lake (CI 16035), Red 33 Lake (CI 17200), Red 4 Lake (CI 14700), Yellow 5 Lake (CI 19140:1), Blue 1 Lake (CI 42090:2).

2 PC

PURE FRESHNESS

HAND SANITIZER & BODY MIST SET

Stay fresh and confident all day with this BCBG Generation Pure Freshness Hand Sanitizer & Body Mist Set. Perfect for on-the-go moments, this duo keeps you feeling clean, refreshed, and lightly fragranced wherever life takes you.

Set Contains:
HAND SANITIZER 40 ML/1.35 FL.OZ

BODY MIST 100 ML/3.38 FL.OZ

Directions: Spray on body throughout the day for a pick-me-up.

Ingredients: Water, Alcohol, PEG-40 Hydrogenated Castor Oil, Fragrance, Glycerin, Propylene Glycol, Phenoxyethanol, Hydrolyzed Collagen, Aloe Barbadensis Leaf Extract, Citrus Aurantium Peel Oil, Tetramethyl Acetyloctahydronaphthalenes, Linalool, Hexyl Cinnamal, Citrus Limon Peel Oil, Benzyl Salicylate, Yellow 5 (CI 19140).

TM/® & © 2024 BCBG IP Holdings LP, used under license.
All rights reserved

Distributed by: Diamond Life Cosmetics Trading FZCO
Address: 6EA G09-SD02-Ground Floor-6 East A, Dubai, U.A.E.
Questions or Comments call (877) 711-8333
Made in China

PHTHALATES FREE

GLUTEN FREE

PARABEN FREE